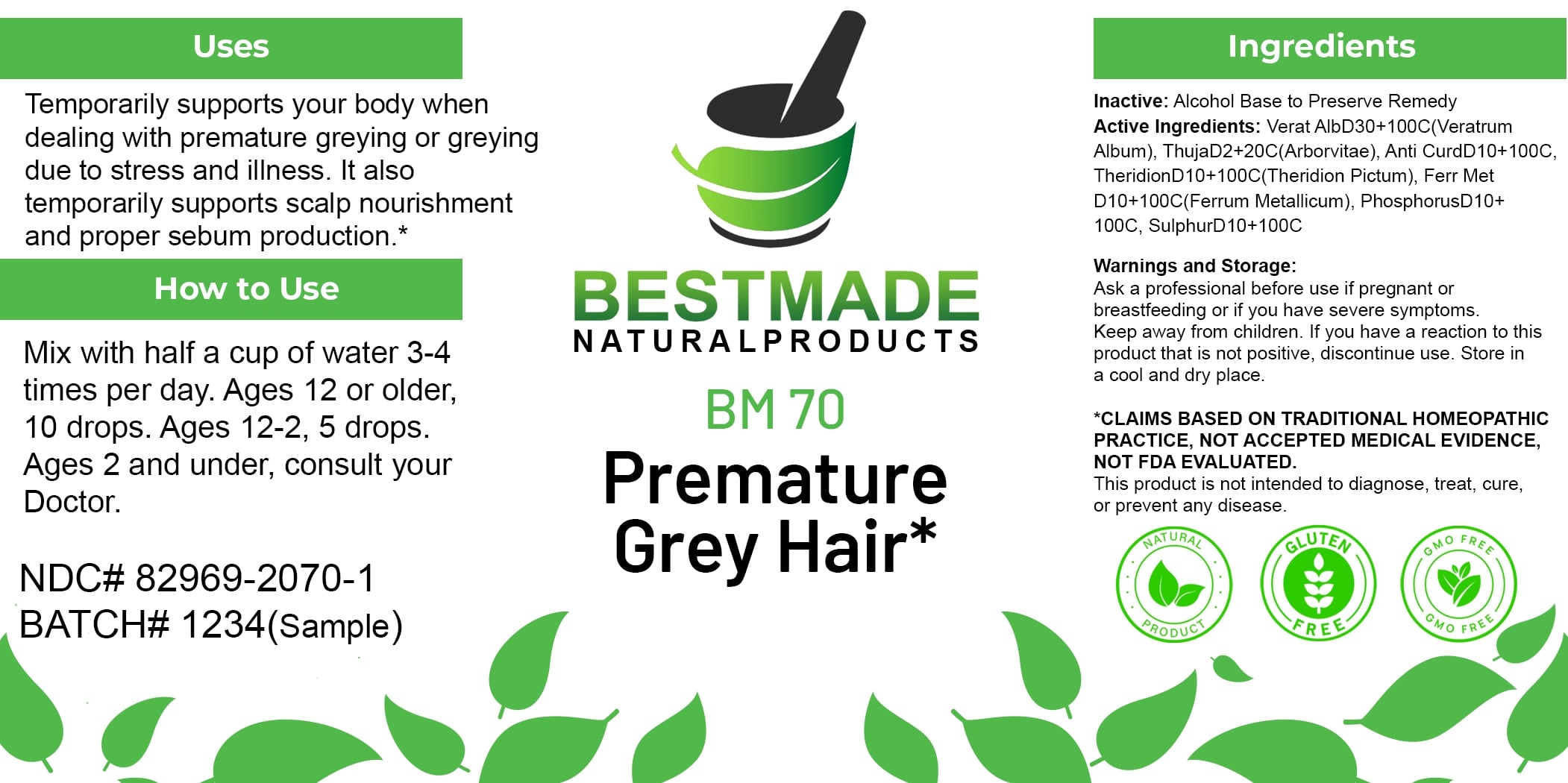 DRUG LABEL: Bestmade Natural Products BM70
NDC: 82969-2070 | Form: LIQUID
Manufacturer: Bestmade Natural Products
Category: homeopathic | Type: HUMAN OTC DRUG LABEL
Date: 20250130

ACTIVE INGREDIENTS: IRON 100 [hp_C]/100 [hp_C]; SULFUR 100 [hp_C]/100 [hp_C]; VERATRUM ALBUM ROOT 100 [hp_C]/100 [hp_C]; THUJA OCCIDENTALIS LEAFY TWIG 100 [hp_C]/100 [hp_C]; THERIDION CURASSAVICUM 100 [hp_C]/100 [hp_C]; PHOSPHORUS 100 [hp_C]/100 [hp_C]; ANTIMONY TRISULFIDE 100 [hp_C]/100 [hp_C]
INACTIVE INGREDIENTS: ALCOHOL 100 [hp_C]/100 [hp_C]

BM70

DOSAGE AND ADMINISTRATION

How to Use

Mix with half a cup of water 3-4 times per day. Ages 12 or older, 10 drops. Ages 12-2, 5 drops. Ages 2 and under, consult your Doctor.

Inactive:

Alcohol Base to Preserve Product

ACTIVE INGREDIENT

Active Ingredients: Verat AlbD30+100C(Veratrum Album), ThujaD2+20C(Arborvitae), Anti CurD10+100C, TheridionD10+100C(Theridion Pictum), Ferr Met D10+100C(Ferrum Metallicum), PhosphorusD10+100C, SulphurD10+100C

Uses

Temporarily supports your body when dealing with premature greying or greying due to stress and illness. It also temporarily supports scalp nourishment and proper sebum production.*

*CLAIMS BASED ON TRADITIONAL HOMEOPATHIC PRACTICE, NOT ACCEPTED MEDICAL EVIDENCE, NOT FDA EVALUATED.

This product is not intended to diagnose, treat, cure, or prevent any disease.

Uses

Temporarily supports your body when dealing with premature greying or greying due to stress and illness. It also temporarily supports scalp nourishment and proper sebum production.*

*CLAIMS BASED ON TRADITIONAL HOMEOPATHIC PRACTICE, NOT ACCEPTED MEDICAL EVIDENCE, NOT FDA EVALUATED.

This product is not intended to diagnose, treat, cure, or prevent any disease.

KEEP OUT OF REACH OF CHILDREN

Warnings and Storage:

Ask a professional before use if pregnant or breastfeeding or if you have severe symptoms. Keep away from children. If you have a reaction to this product that is not positive, discontinue use. Store in a cool and dry place.

Warnings and Storage:

Ask a professional before use if pregnant or breastfeeding or if you have severe symptoms. Keep away from children. If you have a reaction to this product that is not positive, discontinue use. Store in a cool and dry place.

*CLAIMS BASED ON TRADITIONAL HOMEOPATHIC PRACTICE, NOT ACCEPTED MEDICAL EVIDENCE, NOT FDA EVALUATED.

This product is not intended to diagnose, treat, cure, or prevent any disease.

Entire package label